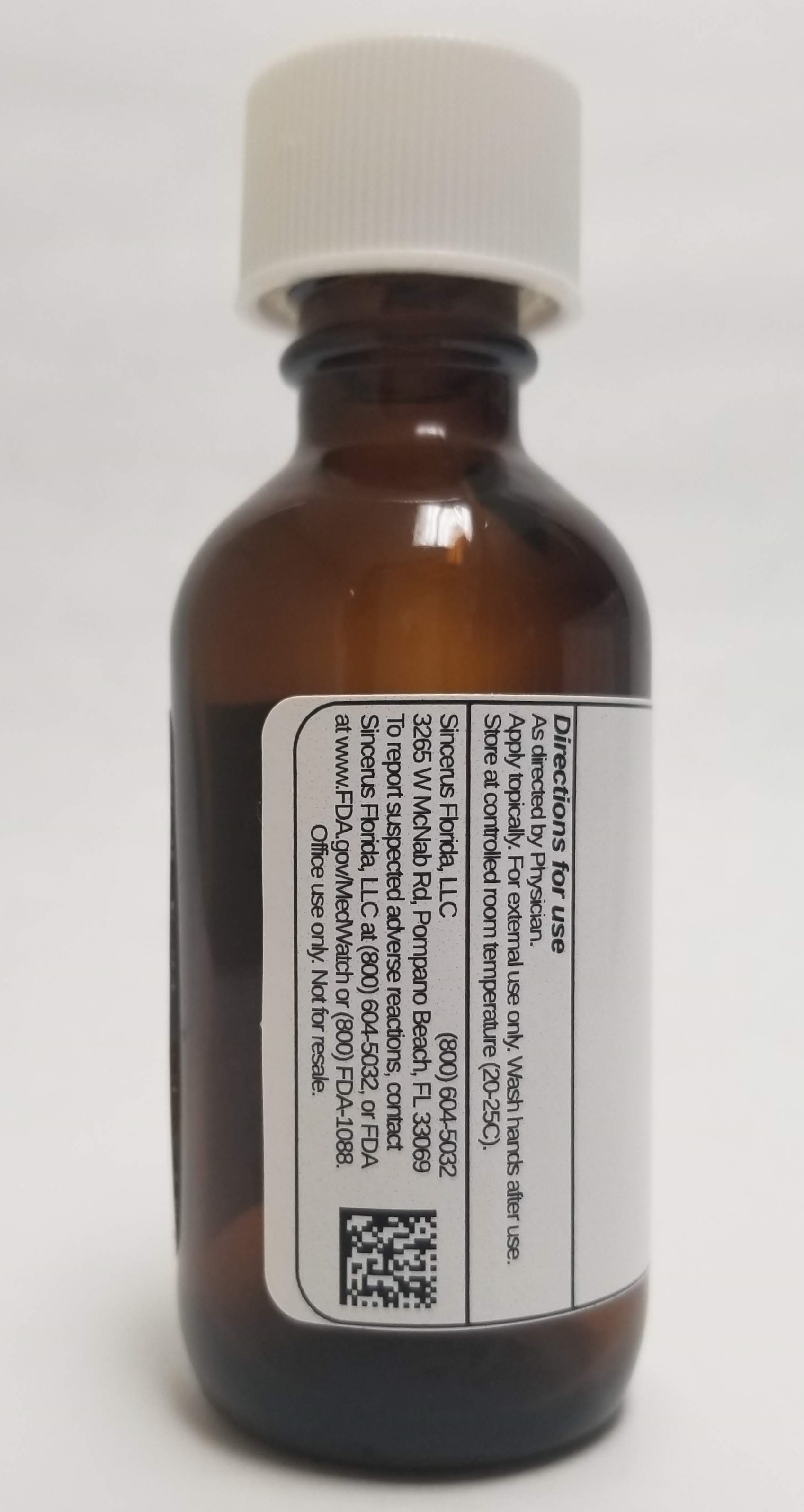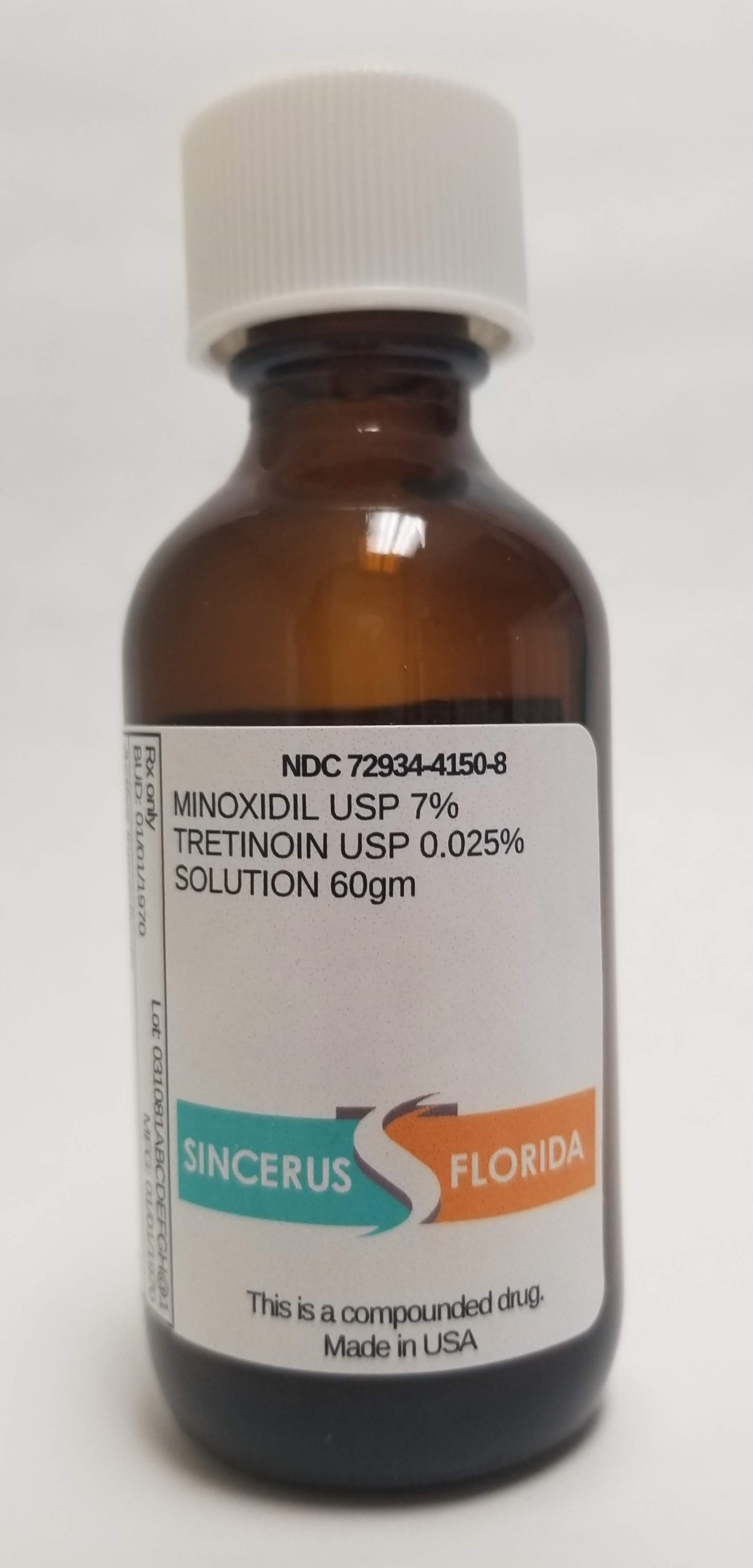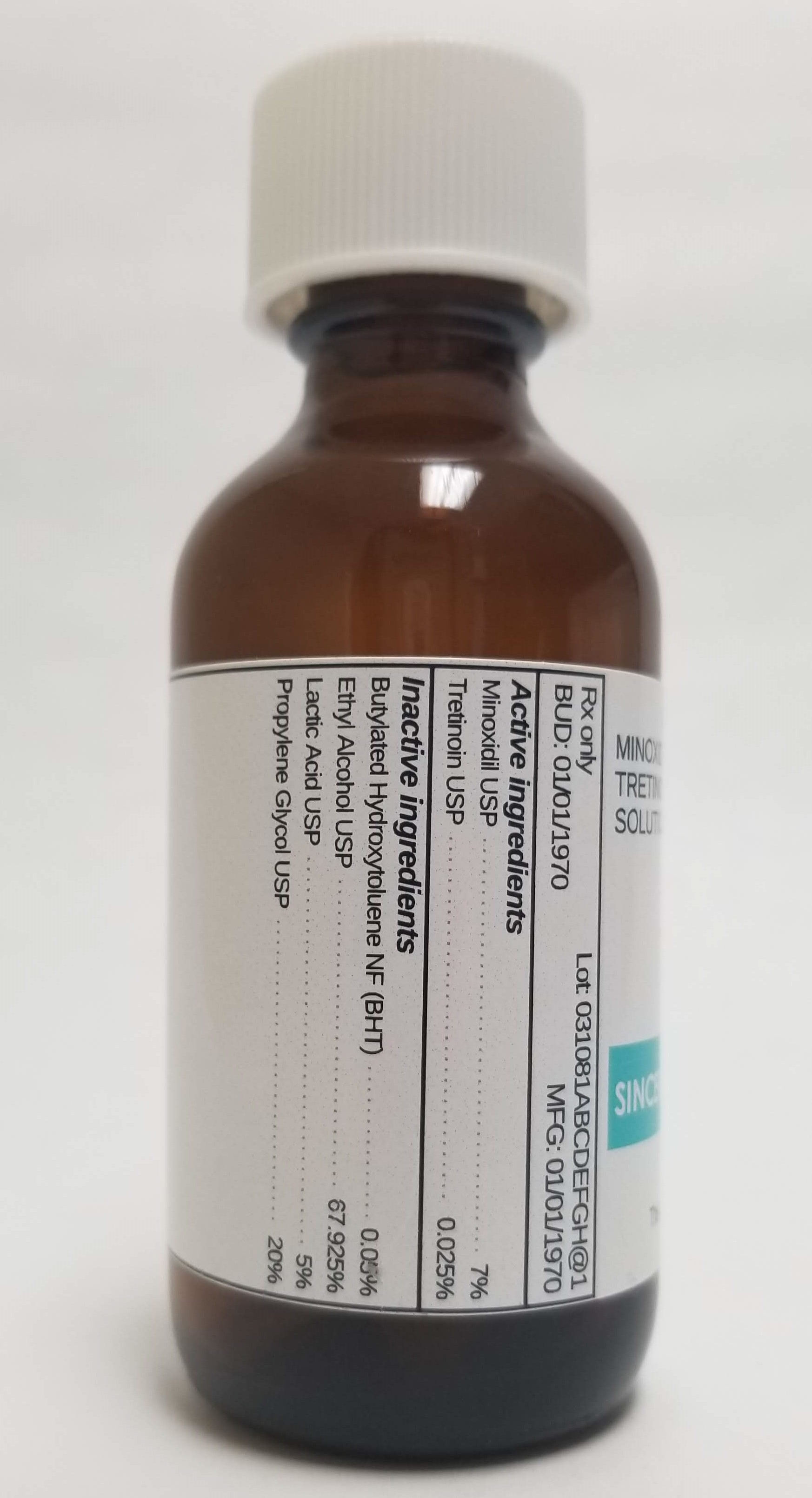 DRUG LABEL: MINOXIDIL 7% / TRETINOIN 0.025%
NDC: 72934-4150 | Form: SOLUTION
Manufacturer: Sincerus Florida, LLC
Category: prescription | Type: HUMAN PRESCRIPTION DRUG LABEL
Date: 20190506

ACTIVE INGREDIENTS: TRETINOIN 0.025 g/100 g; MINOXIDIL 7 g/100 g

MINOXIDIL 7% / TRETINOIN 0.025%